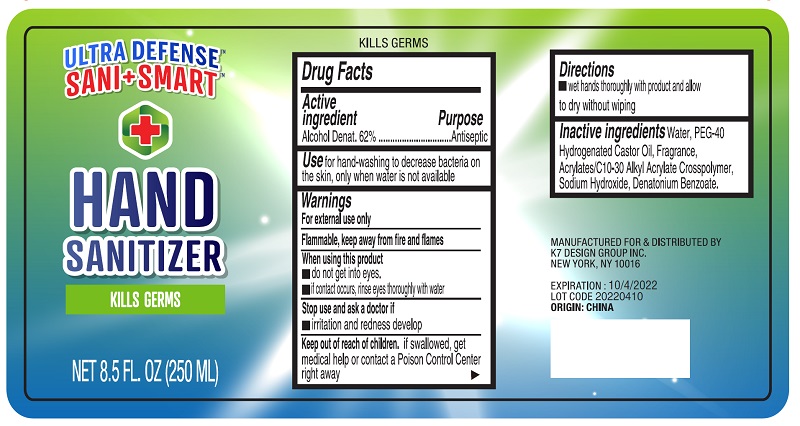 DRUG LABEL: Hand sanitizer
NDC: 70939-003 | Form: GEL
Manufacturer: Dongguang Shuoguo Silicone Products Co., Ltd.
Category: otc | Type: HUMAN OTC DRUG LABEL
Date: 20200506

ACTIVE INGREDIENTS: ALCOHOL 62 mL/100 mL
INACTIVE INGREDIENTS: WATER; PEG-40 STEARATE; GLYCERIN; SODIUM HYDROXIDE; CARBOMER COPOLYMER TYPE A; HYDROGENATED CASTOR OIL

70939-003 62% Alcohol Hand Sanitizer

Active ingredient

Alcohol 62%

Purpose

Antiseptic

Use

Use for hand-washing to decrease bacteria on
the skin, only when water is not available

Warnings

For etemal use only
Flammabl, keep away from fife and fames
When using this poduct
■do not get intoeyes.
iicnacocur, inine eyes hrougwth water
Stop use and aska doctorif
iritation and redness develop

Keep out of reach of children

Keep out of reach of cilden. if sallowed, get
medical help or contact a Poison ControlCenter
right away

Directions

■wethands trougly with poduotd and alw
todry wthout wiping

INACTIVE INGREDIENT

Water, PEG-40
Hydrogenated Castor 0il, Fragrance,
AcylatesC10-30 Alkyl Acrylate Crospolymer,
Sodium Hydroxide, Denatonium Benzoate.